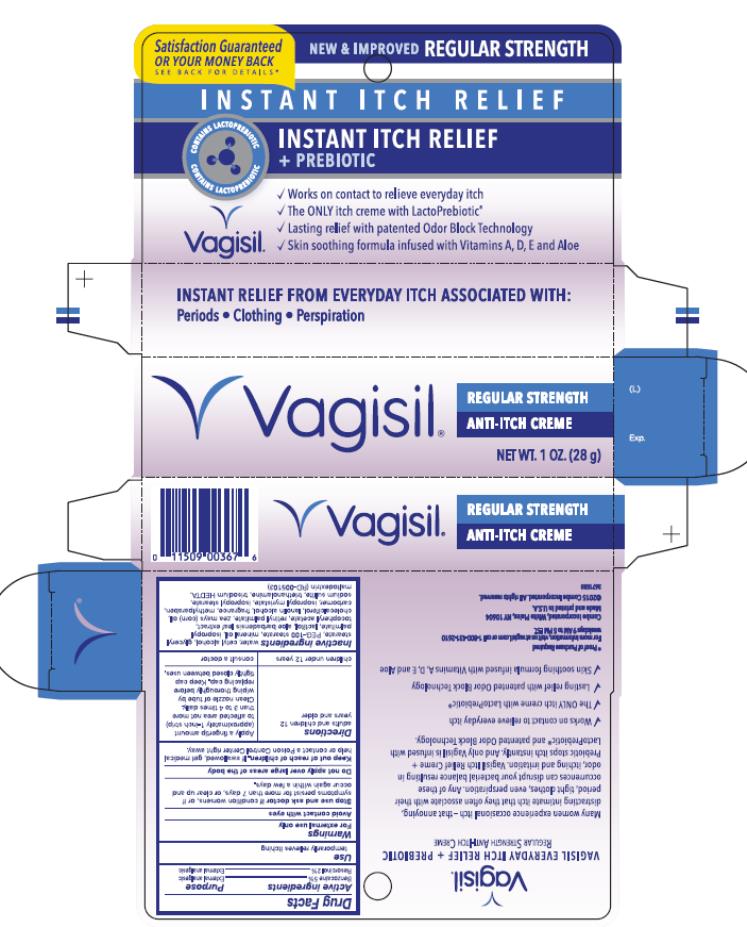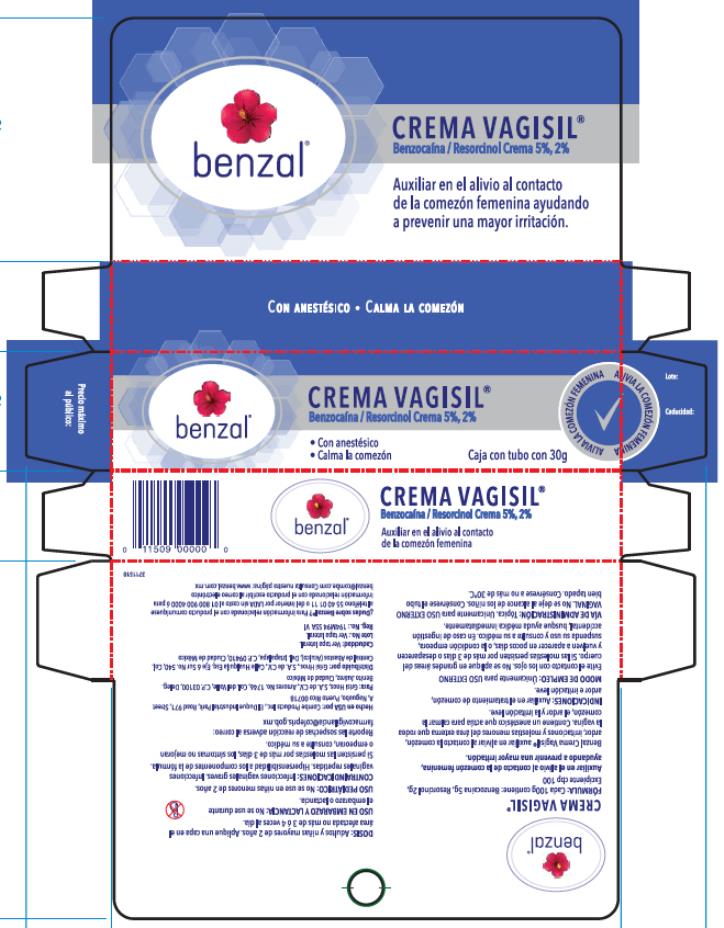 DRUG LABEL: VAGISIL Anti-Itch Creme Regular Strength
NDC: 11509-5103 | Form: CREAM
Manufacturer: Combe Incorporated
Category: otc | Type: HUMAN OTC DRUG LABEL
Date: 20241212

ACTIVE INGREDIENTS: BENZOCAINE 50 mg/1 g; RESORCINOL 20 mg/1 g
INACTIVE INGREDIENTS: WATER; CETYL ALCOHOL; GLYCERYL MONOSTEARATE; PEG-100 MONOSTEARATE; MINERAL OIL; ISOPROPYL PALMITATE; LACTITOL; ALOE VERA LEAF; ALPHA-TOCOPHEROL ACETATE; VITAMIN A PALMITATE; CORN OIL; CHOLECALCIFEROL; LANOLIN ALCOHOLS; METHYLPARABEN; CARBOXYPOLYMETHYLENE; ISOPROPYL MYRISTATE; ISOPROPYL STEARATE; SODIUM SULFITE; TRISODIUM HEDTA; MALTODEXTRIN

Vagisil Regular Strength Anti-Itch Creme

VAGISIL Anti-Itch Creme Regular Strength

Drug Facts

Active ingredient

Benzocaine 5%

Purpose

External analgesic

Active ingredient

Resorcinol 2%

Purpose

External analgesic

Use

temporarily relieves itching

Warnings

For external use only

Avoid contact with eyes

Stop use and ask doctor if

condition worsens, or if symptoms persist for more than 7 days, or clear up and occur again within a few days

Do not apply over large areas of the body

Keep out of reach of children.

If swallowed, get medical

help or contact a Poison Control Center right away.

Directions

adults and children 12 years and older | apply a fingertip amount (approximately 1-inch strip) to affected area not more than 3 to 4 times daily. Clean nozzle of tube by wiping thoroughly before replacing cap. Keep cap tightly closed between uses.
children under 12 years | consult a doctor

Inactive ingredients

Water, Cetyl Alcohol, Glyceryl Stearate, PEG-100 Stearate, Mineral Oil, Isopropyl Palmitate, Lactitol, Aloe Barbadensis Leaf Extract, Tocopheryl Acetate, Retinyl Palmitate, Zea Mays (Corn) Oil, Cholecalciferol, Lanolin Alcohol, Fragrance, Methylparaben, Carbomer, Isopropyl Myristate, Isopropyl Stearate, Sodium Sulfite, Triethanolamine, Trisodium HEDTA, Maltodextrin

PRINCIPAL DISPLAY PANEL

Vagisil
Regular strength Anti Itch Crème
Net Wt. 1 Oz (28 g)

MEXICO

Benzal

Crema Vagisil

Fórmula: Cada 100g contiene: Benzocaina 5g, Resorcinol 2g, Excipiente cbp 100

Auxiliar en el alivio al contacto de la comezón femenina, ayuando a prevenir una mayor irritación.

Benzal Crema Vagisil auxiliar en aliviar al contacto la comezón, ardor, irritaciones y molestias menores del área externa que rodea la vagina. Contiene un anestésico que actúa para calmar la comezón, el ardor y la irritación leve.

Indicaciones: Auxiliar en el tratamiento de comezón, ardor e irritación leve.

Modo de Empleo: Únicamente para USO EXTERNO

Evite el contacto con los ojos. No se aplique en grandes áreas del cuerpo. Si las molestias persisten por más de 3 días o desaparecen y vuelven a aparecer en pocos días, o la condición empeora, suspenda su uso y consulte a su médico. En caso de ingestión accidental, busque ayuda médica inmediamente.

Vía de Administración: Tópica. Unicamente para USO EXTERNO VAGINAL. No se deje al alcance de los niños. Consérvese del tubo bien tapado. Consérvese a no más de 30°C.

Dosis: Adultos y niñas mayores de 2 años. Aplique una capa en el área afectada no más de 3 ó 4 veces al día.

Uso en Embarazo y Lactancia: No se use durante el embarazo o lactancia.

Uso Pediátrico: No se use en niñas menores de 2 años,

Contraindicaciones: Infecciones vaginales graves. Infecciones vaginales repetidas. Hipersensibilidad a los componentes de la fórmula. Si persisten las molestias por más 3 días, los síntomas no mejoran o empeoran, consulte a su médico.

Reporte las sospechas de reacción adversa a correo: farmacovigilancia@cofepris.gob.mx

PRINCIPAL DISPLAY PANEL

Benzal Crema Vagisil

Benzocaína / Resorcinol Crema 5%, 2%

Con anestésico

Calma la comezón

Caja con tubo con 30g